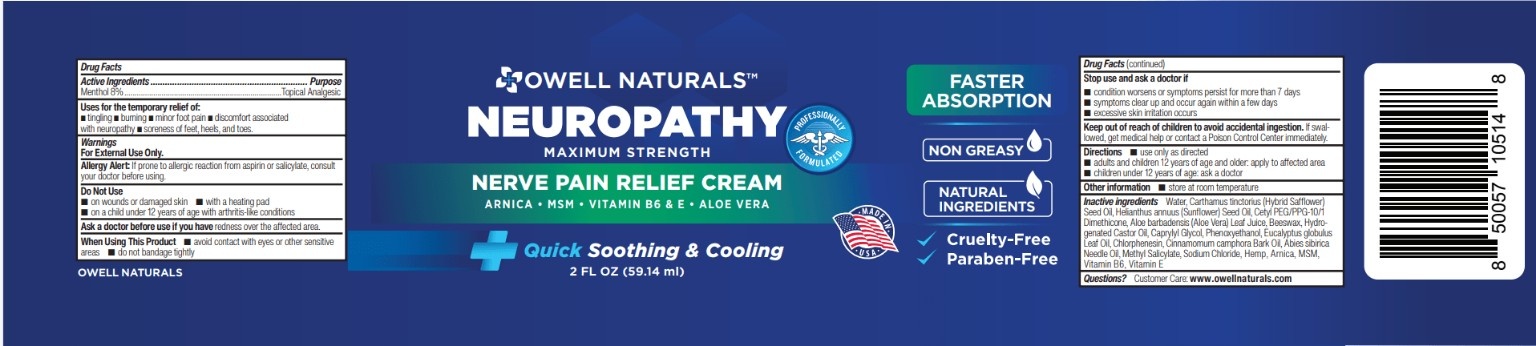 DRUG LABEL: Neuropathy Pain Relief Cream
NDC: 83570-002 | Form: CREAM
Manufacturer: Owell Naturals Brand, LLC
Category: otc | Type: HUMAN OTC DRUG LABEL
Date: 20260117

ACTIVE INGREDIENTS: MENTHOL, UNSPECIFIED FORM 8 g/100 g
INACTIVE INGREDIENTS: WATER 92 g/100 g

Owell Naturals Neuropathy Pain Relief Cream (Menthol) – 2 fl oz

PURPOSE

Menthol 4% ..................................................... Topical analgesic

Active ingredient

Menthol 8% ..................................................... Topical analgesic

using

Temporarily relieves minor aches and pains of muscles and joints associated with arthritis, backache, strains, sprains, and bruises.

Question?

call 1+8453228190

Warnings

For external use only.
Do not use on wounds or damaged skin.
Avoid contact with eyes or mucous membranes.
Do not bandage tightly or use with a heating pad.
Stop use and ask a doctor if condition worsens or symptoms persist for more than 7 days.
Keep out of reach of children.
If swallowed, get medical help or contact a Poison Control Center right away.

Direction

Adults and children 12 years and older:
Apply to affected area not more than 3 to 4 times daily.
Children under 12 years:
Ask a doctor.

Inactive ingredent

Inactive ingredients: Water, Carbomer, Glycerin, Aloe Vera Leaf Juice, Polysorbate 20, Triethanolamine, Arnica, MSM, Vitamin B6, Vitamin E

Indications

Temporarily relieves minor aches and pains of muscles and joints associated with arthritis, backache, strains, sprains, and bruises.

keep out of reach of children

If swallowed, get medical help or contact a Poison Control Center right away.

Dosage and Administration

Apply a thin layer to the affected area up to 3 to 4 times daily.
Massage gently into skin until fully absorbed.
For external use only.

Indications & Usage

For the temporary relief of minor aches and pains of muscles and joints associated with arthritis, backache, strains, sprains, and neuropathic pain.

principle display panel

Oweli Naturals®
Neuropathy Pain Relief Cream
Menthol 8%
Topical Analgesic

Net Wt 2 fl oz (59 mL)

Principal Display Panel

Neuropathy Pain Relief Cream
Menthol 4%
Topical Analgesic
Net Wt 2 fl oz (59 mL)